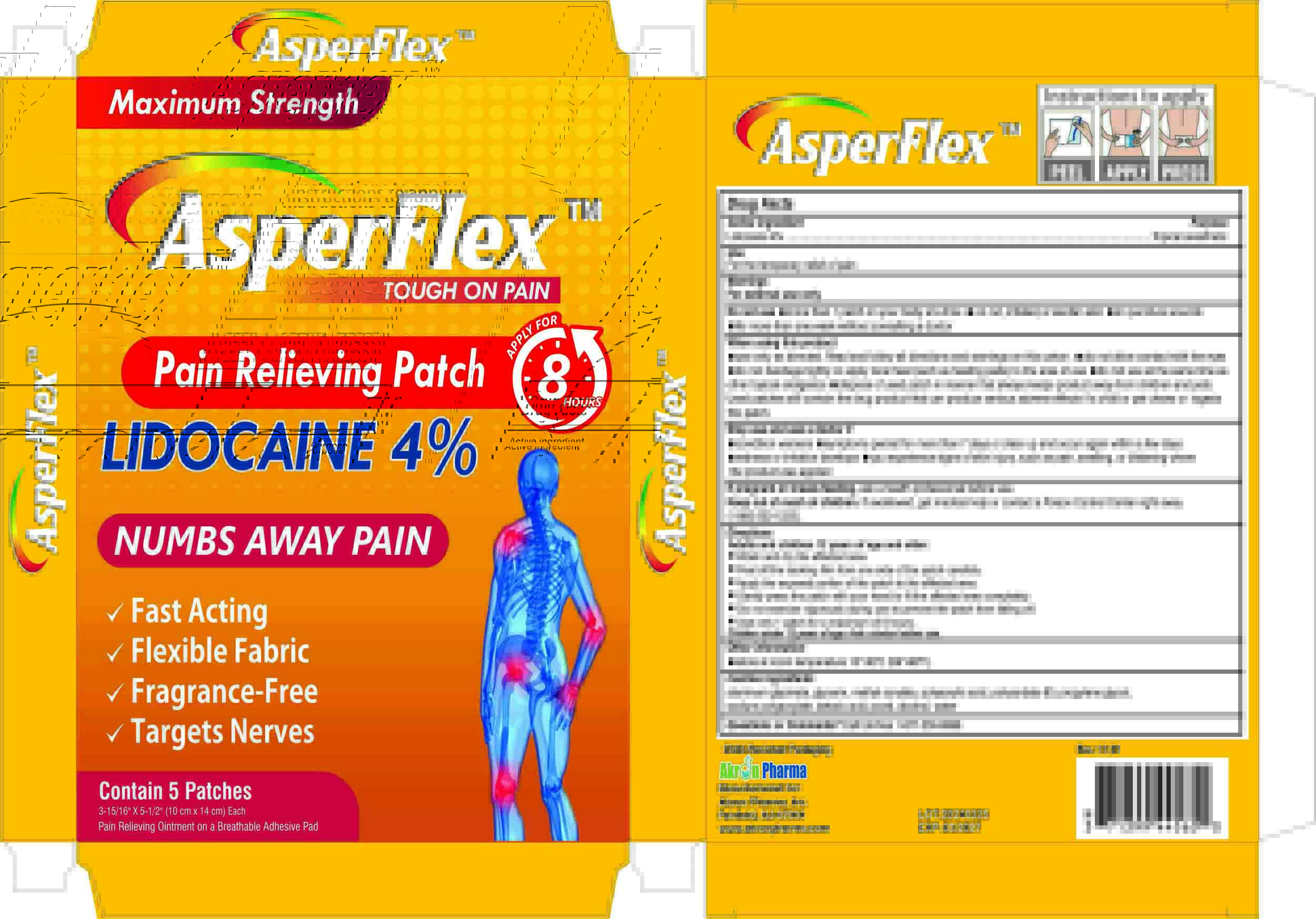 DRUG LABEL: Pain Relieving Patch
NDC: 84273-001 | Form: PATCH
Manufacturer: Hunan En Pu Pharmaceutical Co., Ltd.
Category: otc | Type: HUMAN OTC DRUG LABEL
Date: 20240426

ACTIVE INGREDIENTS: LIDOCAINE 4 g/100 1
INACTIVE INGREDIENTS: TARTARIC ACID; PROPYLENE GLYCOL; POLYVINYL ALCOHOL (18000 MW); ALCOHOL; POLYACRYLIC ACID (250000 MW); SODIUM POLYACRYLATE (2500000 MW); GLYCERIN; METHYL ACRYLATE; DIHYDROXYALUMINUM AMINOACETATE ANHYDROUS; POLYSORBATE 80; WATER

LIDOCAINE PATCH

ACTIVE INGREDIENT

Lidocaine 4%

PURPOSE

Topical anesthetic

INDICATIONS AND USAGE

For the temporary relief of pain

WARNINGS

For external use only

DO NOT USE

more than 1 patch on your body at a time
on cut,irritated,or swollen skin
on puncture wounds
for more than one week without consulting a doctor

WHEN USING

use only as directed. Read and follow all directions and warnings on this carton.
do not allow contact with the eyes
heat (such as heating pads) to the area of use
do not use at the same time as other topical analgesics
dispose of used patch in manner that always keeps product away from children and pets.
Used patches stll contain the drug product that can produce serious adverse effects if a child or pet chews or ingests this patch.

STOP USE

condition worsens
symptoms persist for more than 7 days or clear up and occur again within a few days
redness or irritation develops
you experience signs of skin injury, such as pain, sweling, or blistering where
the product was applied

Keep out of reach of children. lf swallowed, get medical help or contact a Poison Control Center right away

DOSAGE AND ADMINISTRATION

Adults and children 12 years of age and older:
Wash and dry the affected area.
Peel off the backing film from one side of the patch carefully
Apply the exposed portion of the patch to the affected area.
Gently press the patch with your hand to fit the affected area completely.
Do not exercise vigorously during use to prevent the patch from falling off.
Use only 1 patch for a maximum of 8 hours.
Children under 12 years of age: Ask a doctor before use

STORAGE AND HANDLING

store at room temperature 15°-30C (59-86F).

INACTIVE INGREDIENT

aluminum glycinate
glycerin
methyl acrylate
polyacrylic acid
polysorbate 80
propylene glycol
sodium polyacrylate
tartaric acid
poval
alcohol